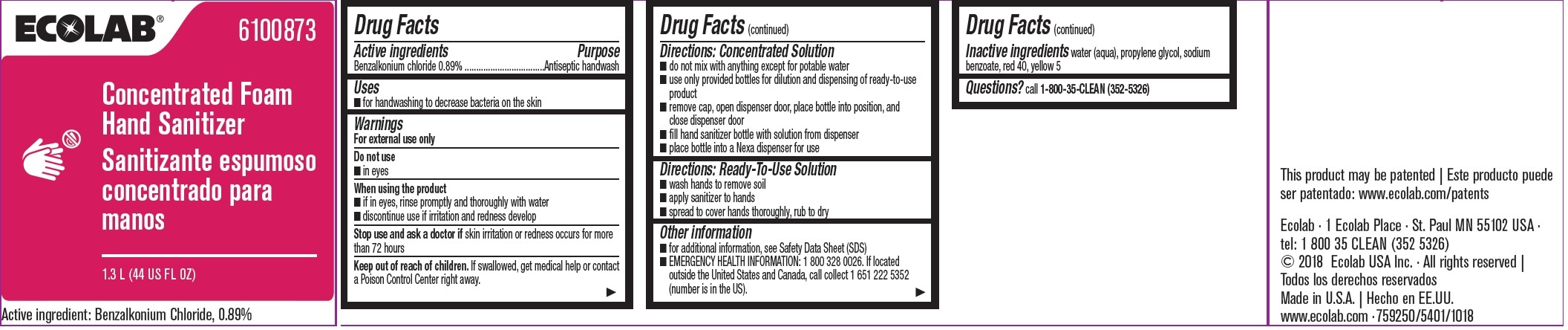 DRUG LABEL: Ecolab Inc.
NDC: 47593-512 | Form: SOLUTION
Manufacturer: Ecolab Inc.
Category: otc | Type: HUMAN OTC DRUG LABEL
Date: 20240531

ACTIVE INGREDIENTS: BENZALKONIUM CHLORIDE 8.9 mg/1 mL
INACTIVE INGREDIENTS: WATER; PROPYLENE GLYCOL; SODIUM BENZOATE; FD&C YELLOW NO. 5; FD&C RED NO. 40

Drug Facts

Active ingredient

Benzalkonium chloride 0.89%

Purpose

Antispetic handwash

Uses

- For handwashing to decrease bacteria on the skin

Warnings

For external use only

Do not use

- In eyes

When using this product

- If in eyes, rinse promptly and thoroughly with water
- discontinue use if irritation and redness develop

Stop use and ask a doctor if skin irritation or redness occurs for more than 72 hours

Keep out of reach of children. If swallowed, get medical help or contact a Posoin Control Center right away.

Directions: Concentrated Solution

- do not mix with anything except for potable water
- use only provided bottles for dilution and dispensing of ready-to-use product
- remove cap, open dispenser door, place bottle into position, and close dispenser door
- fill hand sanitizer bottle with solution form dispenser
- place bottle into a Nexa dispenser for use

Directions: Ready-To-Use Solution

- wash hands to remove soil
- apply sanitizer to hands
- spread to cover hands thoroughly, rub to dry

Other information

- for additional information, see Safety Data Sheet (SDS)
- EMERGENCY HEALTH INFORMATION: 1 800 328 0026. If located outside the United States and Canada, call collect 1 651 222 5352 (number is in the US).

INACTIVE INGREDIENT

Inactive ingredients water (aqua), propylene glycol, sodium benzoate, FD&C yellow 5, FD&C red 40

Questions? call 1-800-35-CLEAN (352-5326)

Principal display panel and representative label

ECOLAB® 6100873

Concentrated Foam1.3 L (44 US FL OZ)

Active ingredient: Benzalkonium chloride, 0.89%

Ecolab - 1 Ecolab Place - St. Paul MN 55102 USA

tel: 1 800 35 CLEAN (352 5326)

© 2018 Ecolab USA Inc • All rights reserved

Made in U.S.A.

www.ecolab.com • 759250/5401/1018